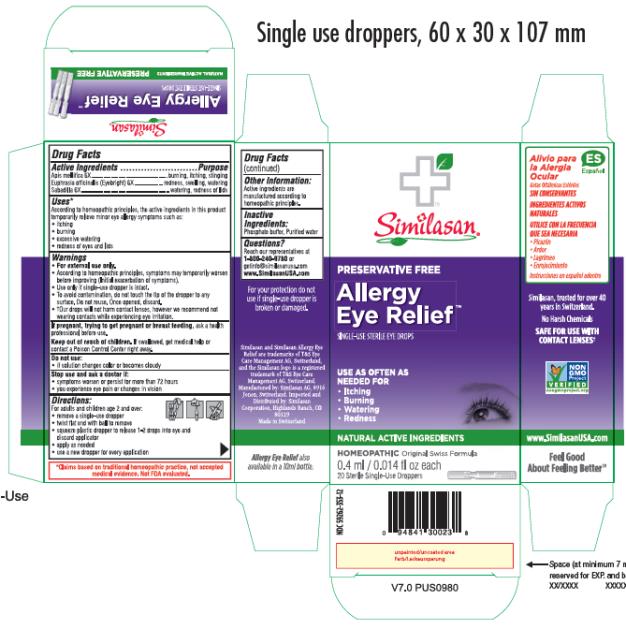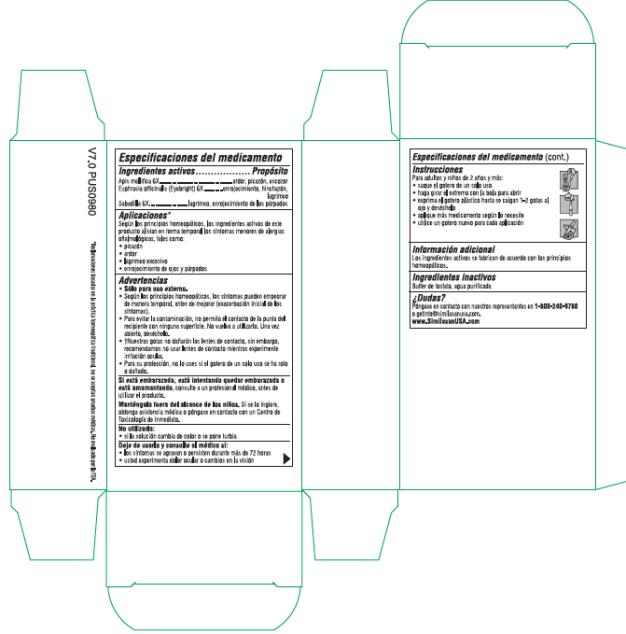 DRUG LABEL: Allergy Eye Relief
NDC: 59262-353 | Form: SOLUTION/ DROPS
Manufacturer: Similasan Corporation
Category: homeopathic | Type: HUMAN OTC DRUG LABEL
Date: 20210428

ACTIVE INGREDIENTS: APIS MELLIFERA 6 [hp_X]/0.4 mL; EUPHRASIA STRICTA 6 [hp_X]/0.4 mL; SCHOENOCAULON OFFICINALE SEED 6 [hp_X]/0.4 mL
INACTIVE INGREDIENTS: WATER; SODIUM PHOSPHATE, MONOBASIC, DIHYDRATE; SODIUM PHOSPHATE, DIBASIC, ANHYDROUS

Allergy Eye Relief, Single Use

Drug Facts

Active Ingredients

Apis mellifica 6X

Euphrasia officinalis (Eyebright) 6X

Sabadilla 6X

Purpose

burning, itching, stinging

redness, swelling, watering

watering, redness of lids

Uses*

According to homeopathic principles, the active ingredients in this product temporarily relieve minor symptoms such as:

• itching

• burning

• excessive watering

- redness of eyes and lids

Warnings

• For external use only.

• According to homeopathic principles, symptoms may temporarily worsen before improving (Initial exacerbation of symptoms).

• Use only if single-use dropper is intact.

• To avoid contamination, do not touch the tip of the dropper to any surface. Do not reuse. Once opened, discard.

• †Our drops will not harm contact lenses, however we recommend not wearing contacts while experiencing eye irritation.

If pregnant, trying to get pregnant or breast feeding,

ask a health professional before use.

Keep out of reach of children.

If swallowed, get medical help or contact a Poison Control Center right away.

Do not use:

• if solution changes color or becomes cloudy

Stop use and ask a doctor if:

• symptoms worsen or persist for more than 72 hours

• you experience eye pain or changes in vision

Directions

For adults and children age 2 and over:

• remove a single-use dropper

• twist flat end with ball to remove

• squeeze plastic dropper to release 1-2 drops into eye and discard applicator

• apply as needed

• use a new dropper for every application

Other Information

Active ingredients are manufactured according to homeopathic principles.

Inactive Ingredients

Phosphate buffer, Purified water

Questions?

Reach our representatives at 1-800-240-9780 or getinfo@similasanusa.com

www.SimilasanUSA.com

PRINCIPAL DISPLAY PANEL

Allergy Eye
Relief

SINGLE-USE STERILE EYE DROPS
0.4 ml/0.014 fl oz each